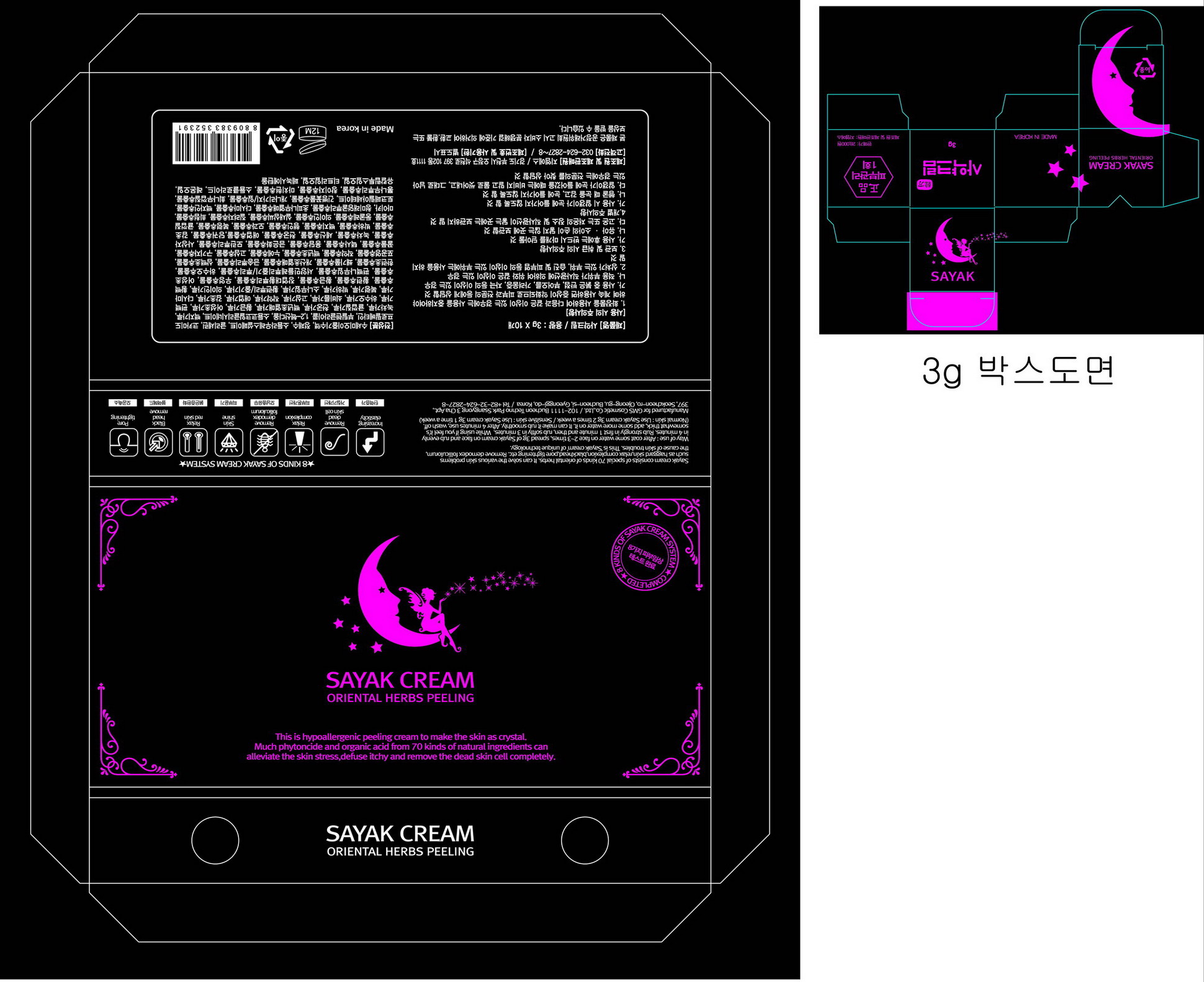 DRUG LABEL: Sayak
NDC: 61884-1001 | Form: CREAM
Manufacturer: GMS 
Category: otc | Type: HUMAN OTC DRUG LABEL
Date: 20140130

ACTIVE INGREDIENTS: GLYCERIN 0.02 g/1 g
INACTIVE INGREDIENTS: SODIUM LAURETH SULFATE; COCAMIDOPROPYL BETAINE; BUTYLENE GLYCOL; 1,2-HEXANEDIOL; ANGELICA DAHURICA ROOT; GREEN TEA LEAF; TANGERINE

Drug Facts

ACTIVE INGREDIENT

glycerin

INACTIVE INGREDIENT

Luffa Cylindrica Stem Sap,Aqua, Sodium Laureth Sulfate, Glycerin,Cocamidopropyl Betaine,Butylene Glycol,1,2-Hexanediol,Sodium Cocoyl Glycinate, Angelica Dahurica Root Powder,Camellia Sinensis Leaf Powder, Citrus Unshiu Peel Powder,Cnidium Officnale Root Powder, Opuntia Coccinellifera Fruit powder, Scutellaria Baicalensis Root Powder,Houttuynia Cordata Powder, Chamaecyparis Obtusa Powder,Polygonum Multiflorum Root Powder, Portulaca Oleracea Powder,Sophora Flavescens Root Powder, Paeonia Albiflora Root Powder,Artemisia Princeps Leaf Powder, Glycyrrhiza Glabra (Licorice) Root Powder, Laminaria Japonica Powder,Poria Cocos Powder, Mentha Arvensis Powder,Pinus Densiflora Leaf Powder, Coptis Chinensis Root/Stalk Powder, Coix Lacryma-Jobi Ma-yuen Seed Powder, Phellodendron Amurense Bark Extract,Coptis Japonica Root Extract, Scutellaria Baicalensis Root Extract,Rheum Palmatum Root Extract, Arctium Lappa Root Extract,Houttuynia Cordata Extract, Chamaecyparis Obtusa Leaf Extract, Taraxacum Officinale (Dandelion) Rhizome/Root Extract, Polygonum Multiflorum Root Extract,Eclipta Prostrata Extract, Urtica Dioica (Nettle) Extract,Zanthoxylum Alatum Fruit Extract, Sciadopitys Verticillata Root Extract,Saururus Chinensis Extract, Taraxacum Platycarpum Extract,Paeonia Albiflora Root Extract, Opuntia occinellifera,Silkworm Extract,Sophora Angustifolia Root Extract, Lycium Chinense Fruit Extract,Prunella Vulgaris Extract, Alisma Orientale Tuber Extract,Gentiana Scabra Root Extract, Lonicera Japonica (Honeysuckle) Flower Extract, Paeonia Suffruticosa Root Extract,Cnidium Monnieri Fruit Extract, Camellia Sinensis Leaf Extract,Asarum Sieboldi Root Extract, Cnidium Officinale Root Extract,Artemisia Princeps Leaf Extract, Angelica Gigas Root Extract,Glycyrrhiza Glabra (Licorice) Root Extract, Mentha Arvensis xtract,Angelica Dahurica Root Extract, Prunus Armeniaca (Apricot) Kernel Extract,Chaenomeles Sinensis Fruit Extract, Poria Cocos Extract,Citrus Unshiu Peel Extract,Polygonatum Odoratum Extract, Coix Lacryma-Jobi Ma-yuen Seed Extract,Cuscuta Australis Seed Extract, Tribulus Terrestris Fruit Extract,Sigesbeckia Orientalis Extract, Mica,Smilax China Root Extract,Zanthoxylum Piperitum Fruit Extract, Laminaria Japonica Extract,Thuja Orientalis Seed Extract,Tocopheryl Acetate, Glechoma Hederacea Extract,Forsythia Koreana Branch/Leaf Extract, Euonymus Sachalinensis Bark Extract,Morus Alba Root Extract, Xanthium Strumarium Fruit Extract,Portulaca Oleracea Extract,Sodium Chloride, Citrus Limon (Lemon) Fruit Oil,Eucalyptus Globulus Leaf Oil, Melaleuca Alternifolia (Tea Tree) Leaf oil, Phenoxyethanol

PURPOSE

to solve the various skin problems such as haggard skin, relax complexion, blackhead, pore tightening
to remove demodex folliculorum the cause of skin troubles

keep out of reach of the children

INDICATIONS AND USAGE

after coat some water on face 2-3 times, spread 3g of Sayak cream on face and rub evenly in 4 minutes
rub strongly in first 1 minute and then rub softly in 3 minutes
while using if you feel it is somewhat thick, add some more water on it which can make it rub smoothly
after 4 minutes use, wash off

stop use if irritation occurs
avoid contact with eyes

DOSAGE AND ADMINISTRATION

for external use only